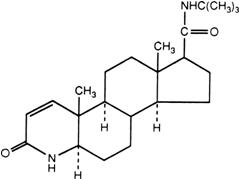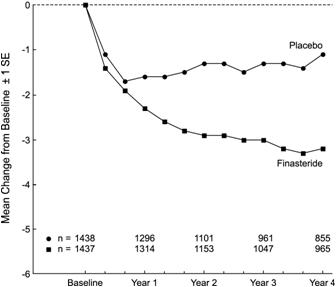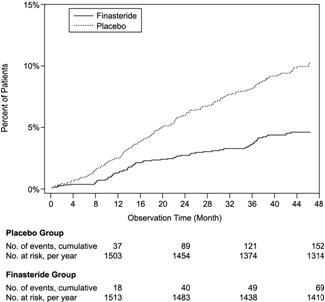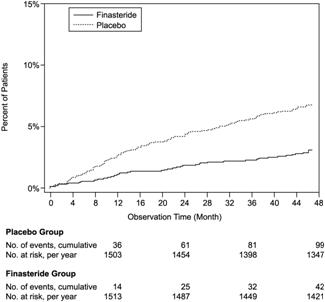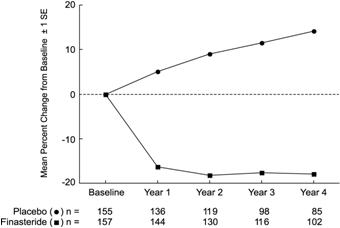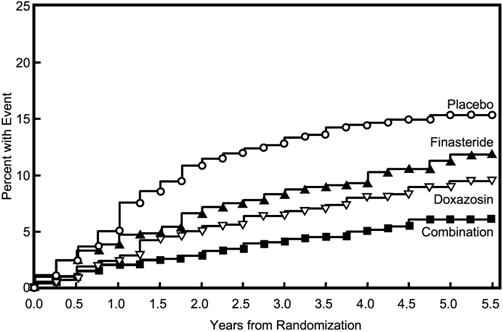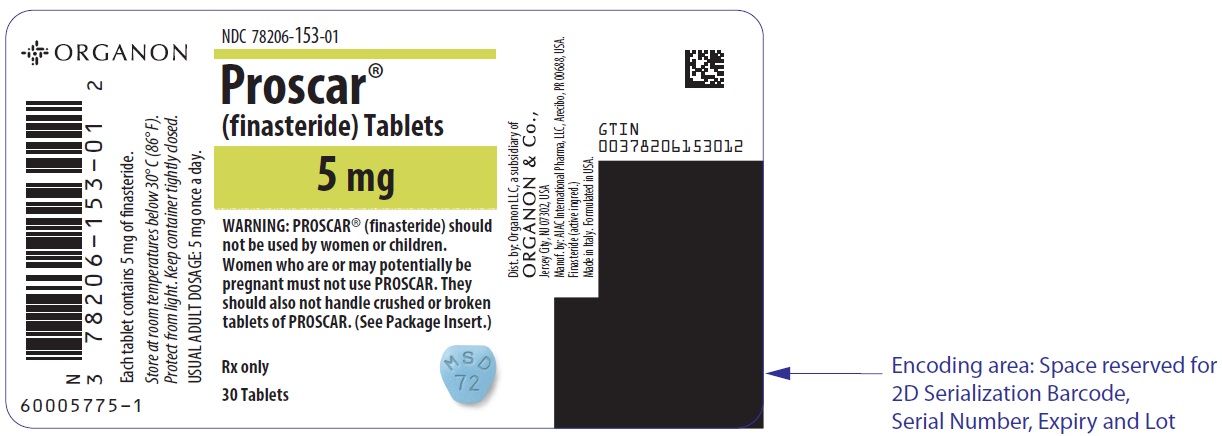 DRUG LABEL: PROSCAR
NDC: 78206-153 | Form: TABLET, FILM COATED
Manufacturer: Organon LLC
Category: prescription | Type: HUMAN PRESCRIPTION DRUG LABEL
Date: 20241223

ACTIVE INGREDIENTS: FINASTERIDE 5 mg/1 1
INACTIVE INGREDIENTS: DOCUSATE SODIUM; FD&C BLUE NO. 2; ALUMINUM OXIDE; LACTOSE MONOHYDRATE; HYDROXYPROPYL CELLULOSE (1600000 WAMW); HYPROMELLOSE, UNSPECIFIED; MAGNESIUM STEARATE; MICROCRYSTALLINE CELLULOSE; STARCH, CORN; SODIUM STARCH GLYCOLATE TYPE A POTATO; TALC; TITANIUM DIOXIDE; FERRIC OXIDE YELLOW

HIGHLIGHTS OF PRESCRIBING INFORMATION

These highlights do not include all the information needed to use PROSCAR safely and effectively. See full prescribing information for PROSCAR.
PROSCAR® (finasteride) Tablets
Initial U.S. Approval: 1992

1 INDICATIONS AND USAGE

PROSCAR, is a 5α-reductase inhibitor, indicated for the treatment of symptomatic benign prostatic hyperplasia (BPH) in men with an enlarged prostate to (1.1):

- Improve symptoms
- Reduce the risk of acute urinary retention
- Reduce the risk of the need for surgery including transurethral resection of the prostate (TURP) and prostatectomy.

PROSCAR administered in combination with the alpha-blocker doxazosin is indicated to reduce the risk of symptomatic progression of BPH (a confirmed ≥4 point increase in American Urological Association (AUA) symptom score) (1.2).

Limitations of Use: PROSCAR is not approved for the prevention of prostate cancer (1.3).

2 DOSAGE AND ADMINISTRATION

PROSCAR may be administered with or without meals (2).

Monotherapy: One tablet (5 mg) taken once a day (2.1).

Combination with Doxazosin: One tablet (5 mg) taken once a day in combination with the alpha-blocker doxazosin (2.2).

3 DOSAGE FORMS AND STRENGTHS

5-mg film-coated tablets (3).

4 CONTRAINDICATIONS

Hypersensitivity to any components of this product (4).

Females who are or may potentially be pregnant (4, 5.3, 8.1, 16).

5 WARNINGS AND PRECAUTIONS

- PROSCAR reduces serum prostate specific antigen (PSA) levels by approximately 50%. However, any confirmed increase in PSA while on PROSCAR may signal the presence of prostate cancer and should be evaluated, even if those values are still within the normal range for men not taking a 5α-reductase inhibitor (5.1).
- PROSCAR may increase the risk of high-grade prostate cancer (5.2, 6.1).
- Females should not handle crushed or broken PROSCAR tablets when they are pregnant or may potentially be pregnant due to potential risk to a male fetus (5.3, 8.1, 16).
- PROSCAR is not indicated for use in pediatric patients or females (5.4, 8.1, 8.2, 8.4, 12.3).
- Prior to initiating treatment with PROSCAR for BPH, consideration should be given to other urological conditions that may cause similar symptoms (5.6).

6 ADVERSE REACTIONS

The drug-related adverse reactions, reported in ≥1% in patients treated with PROSCAR and greater than in patients treated with placebo over a 4-year study are: impotence, decreased libido, decreased volume of ejaculate, breast enlargement, breast tenderness and rash (6.1).

To report SUSPECTED ADVERSE REACTIONS, contact Organon LLC, a subsidiary of Organon & Co., at 1-844-674-3200 or FDA at 1-800-FDA-1088 or www.fda.gov/medwatch.

FULL PRESCRIBING INFORMATION

1 INDICATIONS AND USAGE

1.1 Monotherapy

PROSCAR® is indicated for the treatment of symptomatic benign prostatic hyperplasia (BPH) in men with an enlarged prostate to:

- Improve symptoms
- Reduce the risk of acute urinary retention
- Reduce the risk of the need for surgery including transurethral resection of the prostate (TURP) and prostatectomy.

1.2 Combination with Alpha-Blocker

PROSCAR administered in combination with the alpha-blocker doxazosin is indicated to reduce the risk of symptomatic progression of BPH (a confirmed ≥4 point increase in American Urological Association (AUA) symptom score).

1.3 Limitations of Use

PROSCAR is not approved for the prevention of prostate cancer.

2 DOSAGE AND ADMINISTRATION

PROSCAR may be administered with or without meals.

2.1 Monotherapy

The recommended dose of PROSCAR is one tablet (5 mg) taken once a day [see Clinical Studies (14.1)].

2.2 Combination with Alpha-Blocker

The recommended dose of PROSCAR is one tablet (5 mg) taken once a day in combination with the alpha-blocker doxazosin [see Clinical Studies (14.2)].

3 DOSAGE FORMS AND STRENGTHS

5-mg blue, modified apple-shaped, film-coated tablets, with the code MSD 72 on one side and PROSCAR on the other.

4 CONTRAINDICATIONS

PROSCAR is contraindicated in the following:

- Hypersensitivity to any component of this medication.
- Pregnancy. Finasteride use is contraindicated in females when they are or may potentially be pregnant. Because of the ability of Type II 5α-reductase inhibitors to inhibit the conversion of testosterone to 5α-dihydrotestosterone (DHT), finasteride may cause abnormalities of the external genitalia of a male fetus of a pregnant female who receives finasteride. If this drug is used during pregnancy, or if pregnancy occurs while taking this drug, the pregnant female should be apprised of the potential hazard to the male fetus. [See also Warnings and Precautions (5.3), Use in Specific Populations (8.1), and How Supplied/Storage and Handling (16).] In female rats, low doses of finasteride administered during pregnancy have produced abnormalities of the external genitalia in male offspring.

5 WARNINGS AND PRECAUTIONS

5.1 Effects on Prostate Specific Antigen (PSA) and the Use of PSA in Prostate Cancer Detection

In clinical studies, PROSCAR reduced serum PSA concentration by approximately 50% within six months of treatment. This decrease is predictable over the entire range of PSA values in patients with symptomatic BPH, although it may vary in individuals.

For interpretation of serial PSAs in men taking PROSCAR, a new PSA baseline should be established at least six months after starting treatment and PSA monitored periodically thereafter. Any confirmed increase from the lowest PSA value while on PROSCAR may signal the presence of prostate cancer and should be evaluated, even if PSA levels are still within the normal range for men not taking a 5α-reductase inhibitor. Non-compliance with PROSCAR therapy may also affect PSA test results. To interpret an isolated PSA value in patients treated with PROSCAR for six months or more, PSA values should be doubled for comparison with normal ranges in untreated men. These adjustments preserve the utility of PSA to detect prostate cancer in men treated with PROSCAR.

PROSCAR may also cause decreases in serum PSA in the presence of prostate cancer.

The ratio of free to total PSA (percent free PSA) remains constant even under the influence of PROSCAR. If clinicians elect to use percent free PSA as an aid in the detection of prostate cancer in men undergoing finasteride therapy, no adjustment to its value appears necessary.

5.2 Increased Risk of High-Grade Prostate Cancer

Men aged 55 and over with a normal digital rectal examination and PSA ≤3.0 ng/mL at baseline taking finasteride 5 mg/day in the 7-year Prostate Cancer Prevention Trial (PCPT) had an increased risk of Gleason score 8-10 prostate cancer (finasteride 1.8% vs placebo 1.1%). [See Indications and Usage (1.3) and Adverse Reactions (6.1).] Similar results were observed in a 4-year placebo-controlled clinical trial with another 5α-reductase inhibitor (dutasteride, AVODART) (1% dutasteride vs 0.5% placebo). 5α-reductase inhibitors may increase the risk of development of high-grade prostate cancer. Whether the effect of 5α-reductase inhibitors to reduce prostate volume, or study-related factors, impacted the results of these studies has not been established.

5.3 Exposure of Females — Risk to Male Fetus

PROSCAR is contraindicated in pregnant females and in females who may potentially be pregnant and not indicated for use in females. Based on animal studies and the mechanism of action, PROSCAR may cause abnormal development of external genitalia in a male fetus if administered to a pregnant female. Females who are pregnant or may potentially be pregnant should not handle crushed or broken PROSCAR tablets. PROSCAR tablets are coated and will prevent contact with the active ingredient during normal handling, provided that the tablets have not been broken or crushed. If a pregnant female comes in contact with crushed or broken PROSCAR tablets, the contact area should be washed immediately with soap and water. [See Contraindications (4), Use in Specific Populations (8.1), Clinical Pharmacology (12.1 and 12.3), and How Supplied/Storage and Handling (16).]

5.4 Pediatric Patients and Females

PROSCAR is not indicated for use in pediatric patients [see Use in Specific Populations (8.4) and Clinical Pharmacology (12.3)] or females [see also Warnings and Precautions (5.3), Use in Specific Populations (8.1), Clinical Pharmacology (12.3), and How Supplied/Storage and Handling (16)].

5.5 Effect on Semen Characteristics

Treatment with PROSCAR for 24 weeks to evaluate semen parameters in healthy male volunteers revealed no clinically meaningful effects on sperm concentration, mobility, morphology, or pH. A 0.6 mL (22.1%) median decrease in ejaculate volume with a concomitant reduction in total sperm per ejaculate was observed. These parameters remained within the normal range and were reversible upon discontinuation of therapy with an average time to return to baseline of 84 weeks.

5.6 Consideration of Other Urological Conditions

Prior to initiating treatment with PROSCAR, consideration should be given to other urological conditions that may cause similar symptoms. In addition, prostate cancer and BPH may coexist.

Patients with large residual urinary volume and/or severely diminished urinary flow should be carefully monitored for obstructive uropathy. These patients may not be candidates for finasteride therapy.

6 ADVERSE REACTIONS

6.1 Clinical Trials Experience

Because clinical trials are conducted under widely varying conditions, adverse reaction rates observed in the clinical trials of a drug cannot be directly compared to rates in the clinical trials of another drug and may not reflect the rates observed in clinical practice.

4-Year Placebo-Controlled Study (PLESS)

In PLESS, 1524 patients treated with PROSCAR and 1516 patients treated with placebo were evaluated for safety over a period of 4 years. The most frequently reported adverse reactions were related to sexual function. 3.7% (57 patients) treated with PROSCAR and 2.1% (32 patients) treated with placebo discontinued therapy as a result of adverse reactions related to sexual function, which are the most frequently reported adverse reactions.

Table 1 presents the only clinical adverse reactions considered possibly, probably or definitely drug related by the investigator, for which the incidence on PROSCAR was ≥1% and greater than placebo over the 4 years of the study. In years 2-4 of the study, there was no significant difference between treatment groups in the incidences of impotence, decreased libido and ejaculation disorder.

Table 1: Drug-Related Adverse Experiences
 | Year 1 (%) |  | Years 2, 3 and 4 [Combined Years 2-4] (%)
 | Finasteride | Placebo | Finasteride | Placebo
Impotence | 8.1 | 3.7 | 5.1 | 5.1
Decreased Libido | 6.4 | 3.4 | 2.6 | 2.6
Decreased Volume of Ejaculate | 3.7 | 0.8 | 1.5 | 0.5
Ejaculation Disorder | 0.8 | 0.1 | 0.2 | 0.1
Breast Enlargement | 0.5 | 0.1 | 1.8 | 1.1
Breast Tenderness | 0.4 | 0.1 | 0.7 | 0.3
Rash | 0.5 | 0.2 | 0.5 | 0.1
N = 1524 and 1516, finasteride vs placebo, respectively

Phase III Studies and 5-Year Open Extensions

The adverse experience profile in the 1-year, placebo-controlled, Phase III studies, the 5-year open extensions, and PLESS were similar.

Medical Therapy of Prostatic Symptoms (MTOPS) Study

In the MTOPS study, 3047 men with symptomatic BPH were randomized to receive PROSCAR 5 mg/day (n=768), doxazosin 4 or 8 mg/day (n=756), the combination of PROSCAR 5 mg/day and doxazosin 4 or 8 mg/day (n=786), or placebo (n=737) for 4 to 6 years. [See Clinical Studies (14.2).]

The incidence rates of drug-related adverse experiences reported by ≥2% of patients in any treatment group in the MTOPS Study are listed in Table 2.

The individual adverse effects which occurred more frequently in the combination group compared to either drug alone were: asthenia, postural hypotension, peripheral edema, dizziness, decreased libido, rhinitis, abnormal ejaculation, impotence and abnormal sexual function (see Table 2). Of these, the incidence of abnormal ejaculation in patients receiving combination therapy was comparable to the sum of the incidences of this adverse experience reported for the two monotherapies.

Combination therapy with finasteride and doxazosin was associated with no new clinical adverse experience.

Four patients in MTOPS reported the adverse experience breast cancer. Three of these patients were on finasteride only and one was on combination therapy. [See Long-Term Data.]

The MTOPS Study was not specifically designed to make statistical comparisons between groups for reported adverse experiences. In addition, direct comparisons of safety data between the MTOPS study and previous studies of the single agents may not be appropriate based upon differences in patient population, dosage or dose regimen, and other procedural and study design elements.

Table 2: Incidence ≥2% in One or More Treatment Groups Drug-Related Clinical Adverse Experiences in MTOPS
Adverse Experience | Placebo (N=737) (%) | Doxazosin 4 mg or 8 mg [Doxazosin dose was achieved by weekly titration (1 to 2 to 4 to 8 mg). The final tolerated dose (4 mg or 8 mg) was administered at end-Week 4. Only those patients tolerating at least 4 mg were kept on doxazosin. The majority of patients received the 8-mg dose over the duration of the study.] (N=756) (%) | Finasteride (N=768) (%) | Combination (N=786) (%)
Body as a whole
Asthenia | 7.1 | 15.7 | 5.3 | 16.8
Headache | 2.3 | 4.1 | 2.0 | 2.3
Cardiovascular
Hypotension | 0.7 | 3.4 | 1.2 | 1.5
Postural Hypotension | 8.0 | 16.7 | 9.1 | 17.8
Metabolic and Nutritional
Peripheral Edema | 0.9 | 2.6 | 1.3 | 3.3
Nervous
Dizziness | 8.1 | 17.7 | 7.4 | 23.2
Libido Decreased | 5.7 | 7.0 | 10.0 | 11.6
Somnolence | 1.5 | 3.7 | 1.7 | 3.1
Respiratory
Dyspnea | 0.7 | 2.1 | 0.7 | 1.9
Rhinitis | 0.5 | 1.3 | 1.0 | 2.4
Urogenital
Abnormal Ejaculation | 2.3 | 4.5 | 7.2 | 14.1
Gynecomastia | 0.7 | 1.1 | 2.2 | 1.5
Impotence | 12.2 | 14.4 | 18.5 | 22.6
Sexual Function Abnormal | 0.9 | 2.0 | 2.5 | 3.1

Long-Term Data

High-Grade Prostate Cancer

The PCPT trial was a 7-year randomized, double-blind, placebo-controlled trial that enrolled 18,882 men ≥55 years of age with a normal digital rectal examination and a PSA ≤3.0 ng/mL. Men received either PROSCAR (finasteride 5 mg) or placebo daily. Patients were evaluated annually with PSA and digital rectal exams. Biopsies were performed for elevated PSA, an abnormal digital rectal exam, or the end of study. The incidence of Gleason score 8-10 prostate cancer was higher in men treated with finasteride (1.8%) than in those treated with placebo (1.1%) [see Indications and Usage (1.3) and Warnings and Precautions (5.2)]. In a 4-year placebo-controlled clinical trial with another 5α-reductase inhibitor (dutasteride, AVODART), similar results for Gleason score 8-10 prostate cancer were observed (1% dutasteride vs 0.5% placebo).

No clinical benefit has been demonstrated in patients with prostate cancer treated with PROSCAR.

Breast Cancer

During the 4- to 6-year placebo- and comparator-controlled MTOPS study that enrolled 3047 men, there were 4 cases of breast cancer in men treated with finasteride but no cases in men not treated with finasteride. During the 4-year, placebo-controlled PLESS study that enrolled 3040 men, there were 2 cases of breast cancer in placebo-treated men but no cases in men treated with finasteride. During the 7-year placebo-controlled Prostate Cancer Prevention Trial (PCPT) that enrolled 18,882 men, there was 1 case of breast cancer in men treated with finasteride, and 1 case of breast cancer in men treated with placebo. The relationship between long-term use of finasteride and male breast neoplasia is currently unknown.

Sexual Function

There is no evidence of increased sexual adverse experiences with increased duration of treatment with PROSCAR. New reports of drug-related sexual adverse experiences decreased with duration of therapy.

6.2 Postmarketing Experience

The following additional adverse events have been reported in postmarketing experience with PROSCAR. Because these events are reported voluntarily from a population of uncertain size, it is not always possible to reliably estimate their frequency or establish a causal relationship to drug exposure:

- hypersensitivity reactions, such as pruritus, urticaria, and angioedema (including swelling of the lips, tongue, throat, and face)
- testicular pain
- hematospermia
- sexual dysfunction that continued after discontinuation of treatment, including erectile dysfunction, decreased libido and ejaculation disorders (e.g. reduced ejaculate volume). These events were reported rarely in men taking PROSCAR for the treatment of BPH. Most men were older and were taking concomitant medications and/or had co-morbid conditions. The independent role of PROSCAR in these events is unknown.
- male infertility and/or poor seminal quality were reported rarely in men taking PROSCAR for the treatment of BPH. Normalization or improvement of poor seminal quality has been reported after discontinuation of finasteride. The independent role of PROSCAR in these events is unknown.
- depression
- suicidal ideation
- male breast cancer.

The following additional adverse event related to sexual dysfunction that continued after discontinuation of treatment has been reported in postmarketing experience with finasteride at lower doses used to treat male pattern baldness. Because the event is reported voluntarily from a population of uncertain size, it is not always possible to reliably estimate its frequency or establish a causal relationship to drug exposure:

- orgasm disorders

7 DRUG INTERACTIONS

7.1 Cytochrome P450-Linked Drug Metabolizing Enzyme System

No drug interactions of clinical importance have been identified. Finasteride does not appear to affect the cytochrome P450-linked drug metabolizing enzyme system. Compounds that have been tested in man have included antipyrine, digoxin, propranolol, theophylline, and warfarin and no clinically meaningful interactions were found.

7.2 Other Concomitant Therapy

Although specific interaction studies were not performed, PROSCAR was concomitantly used in clinical studies with acetaminophen, acetylsalicylic acid, α-blockers, angiotensin-converting enzyme (ACE) inhibitors, analgesics, anti-convulsants, beta-adrenergic blocking agents, diuretics, calcium channel blockers, cardiac nitrates, HMG-CoA reductase inhibitors, nonsteroidal anti-inflammatory drugs (NSAIDs), benzodiazepines, H2 antagonists and quinolone anti-infectives without evidence of clinically significant adverse interactions.

8 USE IN SPECIFIC POPULATIONS

8.1 Pregnancy

Risk Summary

PROSCAR is contraindicated in pregnant females and not indicated for use in females. Based on animal studies and the mechanism of action, PROSCAR may cause abnormal development of external genitalia in a male fetus if administered to a pregnant female [see Warnings and Precautions (5.3) and Clinical Pharmacology (12.1)].

In an embryo-fetal development study in rats, there was a dose-dependent increase in hypospadias that occurred in 3.6 to 100% of male offspring of pregnant rats administered oral finasteride during the period of major organogenesis at doses approximately 0.1 to 86 times the maximum recommended human dose (MRHD) of 5 mg/day (based on AUC at animal doses of 0.1 to 100 mg/kg/day). Decreased prostatic and seminal vesicular weights, delayed preputial separation and transient nipple development were also observed in male offspring at oral maternal doses approximately 0.03 times the MRHD (based on AUC at animal dose of 0.03 mg/kg/day), along with decreased anogenital distance in male offspring at oral maternal doses approximately 0.003 times the MRHD (based on AUC at animal dose of 0.003 mg/kg/day).

PROSCAR is a Type II 5α-reductase inhibitor that prevents conversion of testosterone to 5α-dihydrotestosterone (DHT), a hormone necessary for normal development of male genitalia. If this drug is used during pregnancy, or if the patient becomes pregnant while taking this drug, the patient should be apprised of the potential hazard to the male fetus.

Abnormal male genital development is an expected consequence when conversion of testosterone to 5α-dihydrotestosterone (DHT) is inhibited by 5α-reductase inhibitors. These outcomes are similar to those reported in male infants with genetic 5α-reductase deficiency. Females could be exposed to finasteride through contact with crushed or broken PROSCAR tablets or semen from a male partner taking PROSCAR. With regard to finasteride exposure through the skin, PROSCAR tablets are coated and will prevent skin contact with finasteride during normal handling if the tablets have not been crushed or broken. Females who are pregnant or may potentially be pregnant should not handle crushed or broken PROSCAR tablets because of possible exposure of a male fetus. With regard to potential finasteride exposure through semen, three studies have been conducted that measured finasteride concentrations in semen in men receiving PROSCAR 5 mg/day. In these studies the highest amount of finasteride in semen was estimated to be 50- to 100-fold less than the dose of finasteride (5 μg) that had no effect on circulating DHT levels in men [see Data and Clinical Pharmacology (12.3)].

Data

Human Data

In 2 studies of healthy subjects (n=69) receiving PROSCAR 5 mg/day for 6-24 weeks, finasteride concentrations in semen ranged from undetectable (<0.1 ng/mL) to 10.54 ng/mL. In an earlier study using a less sensitive assay, finasteride concentrations in semen of 16 subjects receiving PROSCAR 5 mg/day ranged from undetectable (<1.0 ng/mL) to 21 ng/mL. Using the highest semen level measured and assuming 100% absorption would be up to 105 ng per day, which is 50- to 100-fold less than the dose of finasteride (5 μg) that had no effect on circulating DHT levels in men [see Clinical Pharmacology (12.3)].

Animal Data

In an embryo-fetal development study, pregnant rats received finasteride during the period of major organogenesis (gestation days 6 to 17). At maternal doses of oral finasteride approximately 0.1 to 86 times the maximum recommended human dose (MRHD) of 5 mg/day (based on AUC at animal doses of 0.1 to 100 mg/kg/day) there was a dose-dependent increase in hypospadias that occurred in 3.6 to 100% of male offspring. Exposure multiples were estimated using data from nonpregnant rats. Days 16 to 17 of gestation is a critical period in male fetal rats for differentiation of the external genitalia. At oral maternal doses approximately 0.03 times the MRHD (based on AUC at animal dose of 0.03 mg/kg/day), male offspring had decreased prostatic and seminal vesicular weights, delayed preputial separation and transient nipple development. Decreased anogenital distance occurred in male offspring of pregnant rats that received approximately 0.003 times the MRHD (based on AUC at animal dose of 0.003 mg/kg/day). No abnormalities were observed in female offspring at any maternal dose of finasteride.

No developmental abnormalities were observed in the offspring of untreated females mated with finasteride treated male rats that received approximately 61 times the MRHD (based on AUC at animal dose of 80 mg/kg/day). Slightly decreased fertility was observed in male offspring after administration of about 3 times the MRHD (based on AUC at animal dose of 3 mg/kg/day) to female rats during late gestation and lactation. No effects on fertility were seen in female offspring under these conditions.

No evidence of male external genital malformations or other abnormalities were observed in rabbit fetuses exposed to finasteride during the period of major organogenesis (gestation days 6-18) at maternal oral doses up to 100 mg/kg/day, (finasteride exposure levels were not measured in rabbits). However, this study may not have included the critical period for finasteride effects on development of male external genitalia in the rabbit.

The fetal effects of maternal finasteride exposure during the period of embryonic and fetal development were evaluated in the rhesus monkey (gestation days 20-100), in a species and development period more predictive of specific effects in humans than the studies in rats and rabbits. Intravenous administration of finasteride to pregnant monkeys at doses as high as 800 ng/day (estimated maximal blood concentration of 1.86 ng/mL or about 143 times the highest estimated exposure of pregnant females to finasteride from semen of men taking 5 mg/day) resulted in no abnormalities in male fetuses. In confirmation of the relevance of the rhesus model for human fetal development, oral administration of a dose of finasteride (2 mg/kg/day or approximately 18,000 times the highest estimated blood levels of finasteride from semen of men taking 5 mg/day) to pregnant monkeys resulted in external genital abnormalities in male fetuses. No other abnormalities were observed in male fetuses and no finasteride-related abnormalities were observed in female fetuses at any dose.

8.2 Lactation

Risk Summary

PROSCAR is not indicated for use in females.

8.3 Females and Males of Reproductive Potential

Infertility

Females

PROSCAR is not indicated for use in females.

Males

Treatment with PROSCAR for 24 weeks to evaluate semen parameters in healthy male volunteers revealed no clinically meaningful effects on sperm concentration, mobility, morphology, or pH. A 0.6 mL (22.1%) median decrease in ejaculate volume with a concomitant reduction in total sperm per ejaculate was observed. These parameters remained within the normal range and were reversible upon discontinuation of therapy with an average time to return to baseline of 84 weeks [see Warnings and Precautions (5.5)].

There have been postmarketing reports of male infertility and/or poor seminal quality; normalization or improvement of seminal quality has been reported after discontinuation of finasteride [see Adverse Reactions (6.2)].

8.4 Pediatric Use

PROSCAR is not indicated for use in pediatric patients.

Safety and effectiveness in pediatric patients have not been established.

8.5 Geriatric Use

Of the total number of subjects included in PLESS, 1480 and 105 subjects were 65 and over and 75 and over, respectively. No overall differences in safety or effectiveness were observed between these subjects and younger subjects, and other reported clinical experience has not identified differences in responses between the elderly and younger patients. No dosage adjustment is necessary in the elderly [see Clinical Pharmacology (12.3) and Clinical Studies (14)].

8.6 Hepatic Impairment

Caution should be exercised in the administration of PROSCAR in those patients with liver function abnormalities, as finasteride is metabolized extensively in the liver [see Clinical Pharmacology (12.3)].

8.7 Renal Impairment

No dosage adjustment is necessary in patients with renal impairment [see Clinical Pharmacology (12.3)].

10 OVERDOSAGE

Patients have received single doses of PROSCAR up to 400 mg and multiple doses of PROSCAR up to 80 mg/day for three months without adverse effects. Until further experience is obtained, no specific treatment for an overdose with PROSCAR can be recommended.

Significant lethality was observed in male and female mice at single oral doses of 1500 mg/m^2 (500 mg/kg) and in female and male rats at single oral doses of 2360 mg/m^2 (400 mg/kg) and 5900 mg/m^2 (1000 mg/kg), respectively.

11 DESCRIPTION

PROSCAR (finasteride), a synthetic 4-azasteroid compound, is a specific inhibitor of steroid Type II 5α-reductase, an intracellular enzyme that converts the androgen testosterone into 5α-dihydrotestosterone (DHT).

Finasteride is 4-azaandrost-1-ene-17-carboxamide, N-(1,1-dimethylethyl)-3-oxo-,(5α,17ß)-. The empirical formula of finasteride is C23H36N2O2 and its molecular weight is 372.55. Its structural formula is:

Finasteride is a white crystalline powder with a melting point near 250°C. It is freely soluble in chloroform and in lower alcohol solvents, but is practically insoluble in water.

PROSCAR (finasteride) tablets for oral administration are film-coated tablets that contain 5 mg of finasteride and the following inactive ingredients: hydrous lactose, microcrystalline cellulose, pregelatinized starch, sodium starch glycolate, hydroxypropyl cellulose LF, hydroxypropyl methylcellulose, titanium dioxide, magnesium stearate, talc, docusate sodium, FD&C Blue 2 aluminum lake and yellow iron oxide.

12 CLINICAL PHARMACOLOGY

12.1 Mechanism of Action

The development and enlargement of the prostate gland is dependent on the potent androgen, 5α-dihydrotestosterone (DHT). Type II 5α-reductase metabolizes testosterone to DHT in the prostate gland, liver and skin. DHT induces androgenic effects by binding to androgen receptors in the cell nuclei of these organs.

Finasteride is a competitive and specific inhibitor of Type II 5α-reductase with which it slowly forms a stable enzyme complex. Turnover from this complex is extremely slow (t½ ~ 30 days). This has been demonstrated both in vivo and in vitro. Finasteride has no affinity for the androgen receptor. In man, the 5α-reduced steroid metabolites in blood and urine are decreased after administration of finasteride.

12.2 Pharmacodynamics

In man, a single 5-mg oral dose of PROSCAR produces a rapid reduction in serum DHT concentration, with the maximum effect observed 8 hours after the first dose. The suppression of DHT is maintained throughout the 24-hour dosing interval and with continued treatment. Daily dosing of PROSCAR at 5 mg/day for up to 4 years has been shown to reduce the serum DHT concentration by approximately 70%. The median circulating level of testosterone increased by approximately 10-20% but remained within the physiologic range. In a separate study in healthy men treated with finasteride 1 mg per day (n=82) or placebo (n=69), mean circulating levels of testosterone and estradiol were increased by approximately 15% as compared to baseline, but these remained within the physiologic range.

In patients receiving PROSCAR 5 mg/day, increases of about 10% were observed in luteinizing hormone (LH) and follicle-stimulating hormone (FSH), but levels remained within the normal range. In healthy volunteers, treatment with PROSCAR did not alter the response of LH and FSH to gonadotropin-releasing hormone indicating that the hypothalamic-pituitary-testicular axis was not affected.

In patients with BPH, PROSCAR has no effect on circulating levels of cortisol, prolactin, thyroid-stimulating hormone, or thyroxine. No clinically meaningful effect was observed on the plasma lipid profile (i.e., total cholesterol, low density lipoproteins, high density lipoproteins and triglycerides) or bone mineral density.

Adult males with genetically inherited Type II 5α-reductase deficiency also have decreased levels of DHT. Except for the associated urogenital defects present at birth, no other clinical abnormalities related to Type II 5α-reductase deficiency have been observed in these individuals. These individuals have a small prostate gland throughout life and do not develop BPH.

In patients with BPH treated with finasteride (1-100 mg/day) for 7-10 days prior to prostatectomy, an approximate 80% lower DHT content was measured in prostatic tissue removed at surgery, compared to placebo; testosterone tissue concentration was increased up to 10 times over pretreatment levels, relative to placebo. Intraprostatic content of PSA was also decreased.

In healthy male volunteers treated with PROSCAR for 14 days, discontinuation of therapy resulted in a return of DHT levels to pretreatment levels in approximately 2 weeks. In patients treated for three months, prostate volume, which declined by approximately 20%, returned to close to baseline value after approximately three months of discontinuation of therapy.

12.3 Pharmacokinetics

Absorption

In a study of 15 healthy young subjects, the mean bioavailability of finasteride 5-mg tablets was 63% (range 34-108%), based on the ratio of area under the curve (AUC) relative to an intravenous (IV) reference dose. Maximum finasteride plasma concentration averaged 37 ng/mL (range, 27-49 ng/mL) and was reached 1-2 hours postdose. Bioavailability of finasteride was not affected by food.

Distribution

Mean steady-state volume of distribution was 76 liters (range, 44-96 liters). Approximately 90% of circulating finasteride is bound to plasma proteins. There is a slow accumulation phase for finasteride after multiple dosing. After dosing with 5 mg/day of finasteride for 17 days, plasma concentrations of finasteride were 47 and 54% higher than after the first dose in men 45-60 years old (n=12) and ≥70 years old (n=12), respectively. Mean trough concentrations after 17 days of dosing were 6.2 ng/mL (range, 2.4-9.8 ng/mL) and 8.1 ng/mL (range, 1.8-19.7 ng/mL), respectively, in the two age groups. Although steady state was not reached in this study, mean trough plasma concentration in another study in patients with BPH (mean age, 65 years) receiving 5 mg/day was 9.4 ng/mL (range, 7.1-13.3 ng/mL; n=22) after over a year of dosing.

Finasteride has been shown to cross the blood brain barrier but does not appear to distribute preferentially to the CSF.

In 2 studies of healthy subjects (n=69) receiving PROSCAR 5 mg/day for 6-24 weeks, finasteride concentrations in semen ranged from undetectable (<0.1 ng/mL) to 10.54 ng/mL. In an earlier study using a less sensitive assay, finasteride concentrations in the semen of 16 subjects receiving PROSCAR 5 mg/day ranged from undetectable (<1.0 ng/mL) to 21 ng/mL. Thus, based on a 5-mL ejaculate volume, the amount of finasteride in semen was estimated to be 50- to 100-fold less than the dose of finasteride (5 μg) that had no effect on circulating DHT levels in men [see also Use in Specific Populations (8.1)].

Metabolism

Finasteride is extensively metabolized in the liver, primarily via the cytochrome P450 3A4 enzyme subfamily. Two metabolites, the t-butyl side chain monohydroxylated and monocarboxylic acid metabolites, have been identified that possess no more than 20% of the 5α-reductase inhibitory activity of finasteride.

Excretion

In healthy young subjects (n=15), mean plasma clearance of finasteride was 165 mL/min (range, 70-279 mL/min) and mean elimination half-life in plasma was 6 hours (range, 3-16 hours). Following an oral dose of ^14C-finasteride in man (n=6), a mean of 39% (range, 32-46%) of the dose was excreted in the urine in the form of metabolites; 57% (range, 51-64%) was excreted in the feces.

The mean terminal half-life of finasteride in subjects ≥70 years of age was approximately 8 hours (range, 6-15 hours; n=12), compared with 6 hours (range, 4-12 hours; n=12) in subjects 45-60 years of age. As a result, mean AUC(0-24 hr) after 17 days of dosing was 15% higher in subjects ≥70 years of age than in subjects 45-60 years of age (p=0.02).

Table 3: Mean (SD) Pharmacokinetic Parameters in Healthy Young Subjects (n=15)
 | Mean (± SD)
Bioavailability | 63% (34-108%) [Range]
Clearance (mL/min) | 165 (55)
Volume of Distribution (L) | 76 (14)
Half-Life (hours) | 6.2 (2.1)

Pediatric

Finasteride pharmacokinetics have not been investigated in patients <18 years of age.

Finasteride is not indicated for use in pediatric patients [see Warnings and Precautions (5.4), Use in Specific Populations (8.4)].

Gender

Finasteride is not indicated for use in females [see Contraindications (4), Warnings and Precautions (5.3 and 5.4), Use in Specific Populations (8.1), and How Supplied/Storage and Handling (16)].

Geriatric

No dosage adjustment is necessary in the elderly. Although the elimination rate of finasteride is decreased in the elderly, these findings are of no clinical significance. [See Clinical Pharmacology (12.3) and Use in Specific Populations (8.5).]

Table 4: Mean (SD) Noncompartmental Pharmacokinetic Parameters After Multiple Doses of 5 mg/day in Older Men
 | Mean (± SD)
 | 45-60 years old (n=12) | ≥70 years old (n=12)
AUC (ng•hr/mL) | 389 (98) | 463 (186)
Peak Concentration (ng/mL) | 46.2 (8.7) | 48.4 (14.7)
Time to Peak (hours) | 1.8 (0.7) | 1.8 (0.6)
Half-Life (hours) [First-dose values; all other parameters are last-dose values] | 6.0 (1.5) | 8.2 (2.5)

Race

The effect of race on finasteride pharmacokinetics has not been studied.

Hepatic Impairment

The effect of hepatic impairment on finasteride pharmacokinetics has not been studied. Caution should be exercised in the administration of PROSCAR in those patients with liver function abnormalities, as finasteride is metabolized extensively in the liver.

Renal Impairment

No dosage adjustment is necessary in patients with renal impairment. In patients with chronic renal impairment, with creatinine clearances ranging from 9.0 to 55 mL/min, AUC, maximum plasma concentration, half-life, and protein binding after a single dose of ^14C-finasteride were similar to values obtained in healthy volunteers. Urinary excretion of metabolites was decreased in patients with renal impairment. This decrease was associated with an increase in fecal excretion of metabolites. Plasma concentrations of metabolites were significantly higher in patients with renal impairment (based on a 60% increase in total radioactivity AUC). However, finasteride has been well tolerated in BPH patients with normal renal function receiving up to 80 mg/day for 12 weeks, where exposure of these patients to metabolites would presumably be much greater.

13 NONCLINICAL TOXICOLOGY

13.1 Carcinogenesis, Mutagenesis, Impairment of Fertility

Carcinogenesis

No evidence of a tumorigenic effect was observed in a 24-month study in Sprague-Dawley rats receiving doses of finasteride up to 160 mg/kg/day in males and 320 mg/kg/day in females. These doses produced respective systemic exposure in rats of 111 and 274 times those observed in man receiving the recommended human dose of 5 mg/day. All exposure calculations were based on calculated AUC(0-24 hr) for animals and mean AUC(0-24 hr) for man (0.4 μg•hr/mL).

In a 19-month carcinogenicity study in CD-1 mice, a statistically significant (p≤0.05) increase in the incidence of testicular Leydig cell adenomas was observed at 228 times the human exposure (250 mg/kg/day). In mice at 23 times the human exposure, estimated (25 mg/kg/day) and in rats at 39 times the human exposure (40 mg/kg/day) an increase in the incidence of Leydig cell hyperplasia was observed. A positive correlation between the proliferative changes in the Leydig cells and an increase in serum LH levels (2- to 3-fold above control) has been demonstrated in both rodent species treated with high doses of finasteride. No drug-related Leydig cell changes were seen in either rats or dogs treated with finasteride for 1 year at 30 and 350 times (20 mg/kg/day and 45 mg/kg/day, respectively) or in mice treated for 19 months at 2.3 times the human exposure, estimated (2.5 mg/kg/day).

Mutagenesis

No evidence of mutagenicity was observed in an in vitro bacterial mutagenesis assay, a mammalian cell mutagenesis assay, or in an in vitro alkaline elution assay. In an in vitro chromosome aberration assay, using Chinese hamster ovary cells, there was a slight increase in chromosome aberrations. These concentrations correspond to 4000-5000 times the peak plasma levels in man given a total dose of 5 mg. In an in vivo chromosome aberration assay in mice, no treatment-related increase in chromosome aberration was observed with finasteride at the maximum tolerated dose of 250 mg/kg/day (228 times the human exposure) as determined in the carcinogenicity studies.

Impairment of Fertility

In sexually mature male rabbits treated with finasteride at 543 times the human exposure (80 mg/kg/day) for up to 12 weeks, no effect on fertility, sperm count, or ejaculate volume was seen. In sexually mature male rats treated with 61 times the human exposure (80 mg/kg/day), there were no significant effects on fertility after 6 or 12 weeks of treatment; however, when treatment was continued for up to 24 or 30 weeks, there was an apparent decrease in fertility, fecundity and an associated significant decrease in the weights of the seminal vesicles and prostate. All these effects were reversible within 6 weeks of discontinuation of treatment. No drug-related effect on testes or on mating performance has been seen in rats or rabbits. This decrease in fertility in finasteride-treated rats is secondary to its effect on accessory sex organs (prostate and seminal vesicles) resulting in failure to form a seminal plug. The seminal plug is essential for normal fertility in rats and is not relevant in man.

14 CLINICAL STUDIES

14.1 Monotherapy

PROSCAR 5 mg/day was initially evaluated in patients with symptoms of BPH and enlarged prostates by digital rectal examination in two 1-year, placebo-controlled, randomized, double-blind studies and their 5-year open extensions.

PROSCAR was further evaluated in the PROSCAR Long-Term Efficacy and Safety Study (PLESS), a double-blind, randomized, placebo-controlled, 4-year, multicenter study. 3040 patients between the ages of 45 and 78, with moderate to severe symptoms of BPH and an enlarged prostate upon digital rectal examination, were randomized into the study (1524 to finasteride, 1516 to placebo) and 3016 patients were evaluable for efficacy. 1883 patients completed the 4-year study (1000 in the finasteride group, 883 in the placebo group).

Effect on Symptom Score

Symptoms were quantified using a score similar to the American Urological Association Symptom Score, which evaluated both obstructive symptoms (impairment of size and force of stream, sensation of incomplete bladder emptying, delayed or interrupted urination) and irritative symptoms (nocturia, daytime frequency, need to strain or push the flow of urine) by rating on a 0 to 5 scale for six symptoms and a 0 to 4 scale for one symptom, for a total possible score of 34.

Patients in PLESS had moderate to severe symptoms at baseline (mean of approximately 15 points on a 0-34 point scale). Patients randomized to PROSCAR who remained on therapy for 4 years had a mean (± 1 SD) decrease in symptom score of 3.3 (± 5.8) points compared with 1.3 (± 5.6) points in the placebo group. (See Figure 1.) A statistically significant improvement in symptom score was evident at 1 year in patients treated with PROSCAR vs placebo (–2.3 vs –1.6), and this improvement continued through Year 4.

Figure 1 Symptom Score in PLESS

Results seen in earlier studies were comparable to those seen in PLESS. Although an early improvement in urinary symptoms was seen in some patients, a therapeutic trial of at least 6 months was generally necessary to assess whether a beneficial response in symptom relief had been achieved. The improvement in BPH symptoms was seen during the first year and maintained throughout an additional 5 years of open extension studies.

Effect on Acute Urinary Retention and the Need for Surgery

In PLESS, efficacy was also assessed by evaluating treatment failures. Treatment failure was prospectively defined as BPH-related urological events or clinical deterioration, lack of improvement and/or the need for alternative therapy. BPH-related urological events were defined as urological surgical intervention and acute urinary retention requiring catheterization. Complete event information was available for 92% of the patients. The following table (Table 5) summarizes the results.

Table 5: All Treatment Failures in PLESS
 | Patients (%) [patients with multiple events may be counted more than once for each type of event]
Event | Placebo N=1503 | Finasteride N=1513 | Relative Risk [Hazard ratio based on log rank test] | 95% CI | P Value
All Treatment Failures | 37.1 | 26.2 | 0.68 | (0.57 to 0.79) | <0.001
Surgical Interventions for BPH | 10.1 | 4.6 | 0.45 | (0.32 to 0.63) | <0.001
Acute Urinary Retention Requiring Catheterization | 6.6 | 2.8 | 0.43 | (0.28 to 0.66) | <0.001
Two consecutive symptom scores ≥20 | 9.2 | 6.7
Bladder Stone | 0.4 | 0.5
Incontinence | 2.1 | 1.7
Renal Failure | 0.5 | 0.6
UTI | 5.7 | 4.9
Discontinuation due to worsening of BPH, lack of improvement, or to receive other medical treatment | 21.8 | 13.3

Compared with placebo, PROSCAR was associated with a significantly lower risk for acute urinary retention or the need for BPH-related surgery [13.2% for placebo vs 6.6% for PROSCAR; 51% reduction in risk, 95% CI: (34 to 63%)]. Compared with placebo, PROSCAR was associated with a significantly lower risk for surgery [10.1% for placebo vs 4.6% for PROSCAR; 55% reduction in risk, 95% CI: (37 to 68%)] and with a significantly lower risk of acute urinary retention [6.6% for placebo vs 2.8% for PROSCAR; 57% reduction in risk, 95% CI: (34 to 72%)]; see Figures 2 and 3.

Figure 2 Percent of Patients Having Surgery for BPH, Including TURP

Figure 3 Percent of Patients Developing Acute Urinary Retention (Spontaneous and Precipitated)

Effect on Maximum Urinary Flow Rate

In the patients in PLESS who remained on therapy for the duration of the study and had evaluable urinary flow data, PROSCAR increased maximum urinary flow rate by 1.9 mL/sec compared with 0.2 mL/sec in the placebo group.

There was a clear difference between treatment groups in maximum urinary flow rate in favor of PROSCAR by month 4 (1.0 vs 0.3 mL/sec) which was maintained throughout the study. In the earlier 1-year studies, increase in maximum urinary flow rate was comparable to PLESS and was maintained through the first year and throughout an additional 5 years of open extension studies.

Effect on Prostate Volume

In PLESS, prostate volume was assessed yearly by magnetic resonance imaging (MRI) in a subset of patients. In patients treated with PROSCAR who remained on therapy, prostate volume was reduced compared with both baseline and placebo throughout the 4-year study. PROSCAR decreased prostate volume by 17.9% (from 55.9 cc at baseline to 45.8 cc at 4 years) compared with an increase of 14.1% (from 51.3 cc to 58.5 cc) in the placebo group (p<0.001). (See Figure 4.)

Results seen in earlier studies were comparable to those seen in PLESS. Mean prostate volume at baseline ranged between 40-50 cc. The reduction in prostate volume was seen during the first year and maintained throughout an additional five years of open extension studies.

Figure 4 Prostate Volume in PLESS

Prostate Volume as a Predictor of Therapeutic Response

A meta-analysis combining 1-year data from seven double-blind, placebo-controlled studies of similar design, including 4491 patients with symptomatic BPH, demonstrated that, in patients treated with PROSCAR, the magnitude of symptom response and degree of improvement in maximum urinary flow rate were greater in patients with an enlarged prostate at baseline.

14.2 Combination with Alpha-Blocker Therapy

The Medical Therapy of Prostatic Symptoms (MTOPS) Trial was a double-blind, randomized, placebo-controlled, multicenter, 4- to 6-year study (average 5 years) in 3047 men with symptomatic BPH, who were randomized to receive PROSCAR 5 mg/day (n=768), doxazosin 4 or 8 mg/day (n=756), the combination of PROSCAR 5 mg/day and doxazosin 4 or 8 mg/day (n=786), or placebo (n=737). All participants underwent weekly titration of doxazosin (or its placebo) from 1 to 2 to 4 to 8 mg/day. Only those who tolerated the 4 or 8 mg dose level were kept on doxazosin (or its placebo) in the study. The participant's final tolerated dose (either 4 mg or 8 mg) was administered beginning at end-Week 4. The final doxazosin dose was administered once per day, at bedtime.

The mean patient age at randomization was 62.6 years (±7.3 years). Patients were Caucasian (82%), African American (9%), Hispanic (7%), Asian (1%) or Native American (<1%). The mean duration of BPH symptoms was 4.7 years (±4.6 years). Patients had moderate to severe BPH symptoms at baseline with a mean AUA symptom score of approximately 17 out of 35 points. Mean maximum urinary flow rate was 10.5 mL/sec (±2.6 mL/sec). The mean prostate volume as measured by transrectal ultrasound was 36.3 mL (±20.1 mL). Prostate volume was ≤20 mL in 16% of patients, ≥50 mL in 18% of patients and between 21 and 49 mL in 66% of patients.

The primary endpoint was a composite measure of the first occurrence of any of the following five outcomes: a ≥4 point confirmed increase from baseline in symptom score, acute urinary retention, BPH-related renal insufficiency (creatinine rise), recurrent urinary tract infections or urosepsis, or incontinence. Compared to placebo, treatment with PROSCAR, doxazosin, or combination therapy resulted in a reduction in the risk of experiencing one of these five outcome events by 34% (p=0.002), 39% (p<0.001), and 67% (p<0.001), respectively. Combination therapy resulted in a significant reduction in the risk of the primary endpoint compared to treatment with PROSCAR alone (49%; p≤0.001) or doxazosin alone (46%; p≤0.001). (See Table 6.)

Table 6: Count and Percent Incidence of Primary Outcome Events by Treatment Group in MTOPS
 | Treatment Group
 | Placebo | Doxazosin | Finasteride | Combination | Total
 | N=737 | N=756 | N=768 | N=786 | N=3047
Event | N (%) | N (%) | N (%) | N (%) | N (%)
AUA 4-point rise | 100 (13.6) | 59 (7.8) | 74 (9.6) | 41 (5.2) | 274 (9.0)
Acute urinary retention | 18 (2.4) | 13 (1.7) | 6 (0.8) | 4 (0.5) | 41 (1.3)
Incontinence | 8 (1.1) | 11 (1.5) | 9 (1.2) | 3 (0.4) | 31 (1.0)
Recurrent UTI/urosepsis | 2 (0.3) | 2 (0.3) | 0 (0.0) | 1 (0.1) | 5 (0.2)
Creatinine rise | 0 (0.0) | 0 (0.0) | 0 (0.0) | 0 (0.0) | 0 (0.0)
Total Events | 128 (17.4) | 85 (11.2) | 89 (11.6) | 49 (6.2) | 351 (11.5)

The majority of the events (274 out of 351; 78%) was a confirmed ≥4 point increase in symptom score, referred to as symptom score progression. The risk of symptom score progression was reduced by 30% (p=0.016), 46% (p<0.001), and 64% (p<0.001) in patients treated with PROSCAR, doxazosin, or the combination, respectively, compared to patients treated with placebo (see Figure 5). Combination therapy significantly reduced the risk of symptom score progression compared to the effect of PROSCAR alone (p<0.001) and compared to doxazosin alone (p=0.037).

Figure 5 Cumulative Incidence of a 4-Point Rise in AUA Symptom Score by Treatment Group

Treatment with PROSCAR, doxazosin or the combination of PROSCAR with doxazosin, reduced the mean symptom score from baseline at year 4. Table 7 provides the mean change from baseline for AUA symptom score by treatment group for patients who remained on therapy for four years.

Table 7: Change From Baseline in AUA Symptom Score by Treatment Group at Year 4 in MTOPS
 | Placebo N=534 | Doxazosin N=582 | Finasteride N=565 | Combination N=598
Baseline Mean (SD) | 16.8 (6.0) | 17.0 (5.9) | 17.1 (6.0) | 16.8 (5.8)
Mean Change AUA Symptom Score (SD) | -4.9 (5.8) | -6.6 (6.1) | -5.6 (5.9) | -7.4 (6.3)
Comparison to Placebo (95% CI) |  | -1.8 (-2.5, -1.1) | -0.7 (-1.4, 0.0) | -2.5 (-3.2, -1.8)
Comparison to Doxazosin alone (95% CI) |  |  |  | -0.7 (-1.4, 0.0)
Comparison to Finasteride alone (95% CI) |  |  |  | -1.8 (-2.5, -1.1)

The results of MTOPS are consistent with the findings of the 4-year, placebo-controlled study PLESS [see Clinical Studies (14.1)] in that treatment with PROSCAR reduces the risk of acute urinary retention and the need for BPH-related surgery. In MTOPS, the risk of developing acute urinary retention was reduced by 67% in patients treated with PROSCAR compared to patients treated with placebo (0.8% for PROSCAR and 2.4% for placebo). Also, the risk of requiring BPH-related invasive therapy was reduced by 64% in patients treated with PROSCAR compared to patients treated with placebo (2.0% for PROSCAR and 5.4% for placebo).

14.3 Summary of Clinical Studies

The data from these studies, showing improvement in BPH-related symptoms, reduction in treatment failure (BPH-related urological events), increased maximum urinary flow rates, and decreasing prostate volume, suggest that PROSCAR arrests the disease process of BPH in men with an enlarged prostate.

16 HOW SUPPLIED/STORAGE AND HANDLING

PROSCAR tablets 5 mg are blue, modified apple-shaped, film-coated tablets, with the code MSD 72 on one side and PROSCAR on the other. They are supplied as follows:

NDC 78206-153-01 unit of use bottles of 30

NDC 78206-153-02 unit of use bottles of 100.

Storage and Handling

Store at room temperatures below 30°C (86°F). Protect from light and keep container tightly closed.

Females should not handle crushed or broken PROSCAR tablets when they are pregnant or may potentially be pregnant because of the possibility of absorption of finasteride and the subsequent potential risk to a male fetus [see Warnings and Precautions (5.3) and Use in Specific Populations (8.1)].

17 PATIENT COUNSELING INFORMATION

Advise the patient to read the FDA-approved patient labeling (Patient Information).

Increased Risk of High-Grade Prostate Cancer

Patients should be informed that there was an increase in high-grade prostate cancer in men treated with 5α-reductase inhibitors indicated for BPH treatment, including PROSCAR, compared to those treated with placebo in studies looking at the use of these drugs to prevent prostate cancer [see Indications and Usage (1.3), Warnings and Precautions (5.2), and Adverse Reactions (6.1)].

Exposure of Females — Risk to Male Fetus

Physicians should inform patients that females who are pregnant or may potentially be pregnant should not handle crushed or broken PROSCAR tablets because of the possibility of absorption of finasteride and the subsequent potential risk to the male fetus. PROSCAR tablets are coated and will prevent contact with the active ingredient during normal handling, provided that the tablets have not been broken or crushed. If a female who is pregnant or may potentially be pregnant comes in contact with crushed or broken PROSCAR tablets, the contact area should be washed immediately with soap and water [see Contraindications (4), Warnings and Precautions (5.3), Use in Specific Populations (8.1) and How Supplied/Storage and Handling (16)].

Additional Instructions

Physicians should inform patients that the volume of ejaculate may be decreased in some patients during treatment with PROSCAR. This decrease does not appear to interfere with normal sexual function. However, impotence and decreased libido may occur in patients treated with PROSCAR [see Adverse Reactions (6.1)].

Physicians should instruct their patients to promptly report any changes in their breasts such as lumps, pain or nipple discharge. Breast changes including breast enlargement, tenderness and neoplasm have been reported [see Adverse Reactions (6.1)].

Physicians should instruct their patients to read the patient package insert before starting therapy with PROSCAR and to reread it each time the prescription is renewed so that they are aware of current information for patients regarding PROSCAR.

Dist. by: Organon LLC, a subsidiary of
ORGANON & Co.,
Jersey City, NJ 07302, USA

For patent information: www.organon.com/our-solutions/patent/

© 2023 Organon group of companies. All rights reserved.

uspi-og0906-5t-2311r003

PATIENT INFORMATION

PROSCAR® (finasteride) Tablets
Patient Information about
PROSCAR® (Prahs-car)
Generic name: finasteride
(fin-AS-tur-eyed)

PROSCAR is for use by men only.

Please read this leaflet before you start taking PROSCAR. Also, read it each time you renew your prescription, just in case anything has changed. Remember, this leaflet does not take the place of careful discussions with your doctor. You and your doctor should discuss PROSCAR when you start taking your medication and at regular checkups.

What is PROSCAR?

PROSCAR is a medication used to treat symptoms of benign prostatic hyperplasia (BPH) in men with an enlarged prostate. PROSCAR may also be used to reduce the risk of a sudden inability to pass urine and the need for surgery related to BPH in men with an enlarged prostate.

PROSCAR may be prescribed along with another medicine, an alpha-blocker called doxazosin, to help you better manage your BPH symptoms.

Who should NOT take PROSCAR?

PROSCAR is for use by MEN only.

Do Not Take PROSCAR if you are:

- a woman who is pregnant or may potentially be pregnant. PROSCAR may harm your unborn baby. Do not touch or handle crushed or broken PROSCAR tablets (see "A warning about PROSCAR and pregnancy").
- allergic to finasteride or any of the ingredients in PROSCAR. See the end of this leaflet for a complete list of ingredients in PROSCAR.

A warning about PROSCAR and pregnancy:

Women who are or may potentially be pregnant must not use PROSCAR. They should also not handle crushed or broken tablets of PROSCAR. PROSCAR tablets are coated and will prevent contact with the active ingredient during normal handling, provided that the tablets are not broken or crushed.

If a woman who is pregnant with a male baby absorbs the active ingredient in PROSCAR after oral use or through the skin, it may cause the male baby to be born with abnormalities of the sex organs. If a woman who is pregnant comes into contact with the active ingredient in PROSCAR, a doctor should be consulted.

How should I take PROSCAR?

Follow your doctor's instruction.

- Take one tablet by mouth each day. To avoid forgetting to take PROSCAR, you can take it at the same time every day.
- If you forget to take PROSCAR, do not take an extra tablet. Just take the next tablet as usual.
- You may take PROSCAR with or without food.
- Do not share PROSCAR with anyone else; it was prescribed only for you.

What are the possible side effects of PROSCAR?

PROSCAR may increase the chance of a more serious form of prostate cancer.

The most common side effects of PROSCAR include:

- trouble getting or keeping an erection (impotence)
- decrease in sex drive
- decreased volume of ejaculate
- ejaculation disorders
- enlarged or painful breast. You should promptly report to your doctor any changes in your breasts such as lumps, pain or nipple discharge.

The following have been reported in general use with PROSCAR and/or finasteride at lower doses:

- allergic reactions, including rash, itching, hives, and swelling of the lips, tongue, throat, and face
- rarely, some men may have testicular pain
- blood in semen
- trouble getting or keeping an erection that continued after stopping the medication
- problems with ejaculation that continued after stopping the medication
- male infertility and/or poor quality of semen. Improvement in the quality of semen has been reported after stopping the medication.
- depression
- suicidal thoughts
- decrease in sex drive that continued after stopping the medication
- in rare cases, male breast cancer has been reported.

You should discuss side effects with your doctor before taking PROSCAR and anytime you think you are having a side effect. These are not all the possible side effects with PROSCAR. For more information, ask your doctor or pharmacist.

Call your doctor for medical advice about side effects. You may report side effects to FDA at: 1-800-FDA-1088.

What you need to know while taking PROSCAR:

- You should see your doctor regularly while taking PROSCAR. Follow your doctor's advice about when to have these checkups.
- Checking for prostate cancer. Your doctor has prescribed PROSCAR for BPH and not for treatment of prostate cancer — but a man can have BPH and prostate cancer at the same time. Your doctor may continue checking for prostate cancer while you take PROSCAR.
- About Prostate-Specific Antigen (PSA). Your doctor may have done a blood test called PSA for the screening of prostate cancer. Because PROSCAR decreases PSA levels, you should tell your doctor(s) that you are taking PROSCAR. Changes in PSA levels will need to be evaluated by your doctor(s). Any increase in follow-up PSA levels from their lowest point may signal the presence of prostate cancer and should be evaluated, even if the test results are still within the normal range. You should also tell your doctor if you have not been taking PROSCAR as prescribed because this may affect the PSA test results. For more information, talk to your doctor.

How should I store PROSCAR?

- Store PROSCAR tablets in a dry place at room temperature.
- Keep PROSCAR in the original container and keep the container closed.
  PROSCAR tablets are coated and will prevent contact with the active ingredient during normal handling, provided that the tablets are not broken or crushed.

Keep PROSCAR and all medications out of the reach of children.

Do not give your PROSCAR tablets to anyone else. It has been prescribed only for you.

For more information call 1-844-674-3200.

What are the ingredients in PROSCAR?

Active ingredients: finasteride

Inactive ingredients: hydrous lactose, microcrystalline cellulose, pregelatinized starch, sodium starch glycolate, hydroxypropyl cellulose LF, hydroxypropyl methylcellulose, titanium dioxide, magnesium stearate, talc, docusate sodium, FD&C Blue 2 aluminum lake and yellow iron oxide.

What is BPH?

BPH is an enlargement of the prostate gland. The prostate is located below the bladder. As the prostate enlarges, it may slowly restrict the flow of urine. This can lead to symptoms such as:

- a weak or interrupted urinary stream
- a feeling that you cannot empty your bladder completely
- a feeling of delay or hesitation when you start to urinate
- a need to urinate often, especially at night
- a feeling that you must urinate right away.

In some men, BPH can lead to serious problems, including urinary tract infections, a sudden inability to pass urine (acute urinary retention), as well as the need for surgery.

What PROSCAR does:

PROSCAR lowers levels of a hormone called DHT (dihydrotestosterone), which is a cause of prostate growth. Lowering DHT leads to shrinkage of the enlarged prostate gland in most men. This can lead to gradual improvement in urine flow and symptoms over the next several months. PROSCAR will help reduce the risk of developing a sudden inability to pass urine and the need for surgery related to an enlarged prostate. However, since each case of BPH is different, you should know that:

- Even though the prostate shrinks, you may NOT notice an improvement in urine flow or symptoms.
- You may need to take PROSCAR for six (6) months or more to see whether it improves your symptoms.
- Therapy with PROSCAR may reduce your risk for a sudden inability to pass urine and the need for surgery for an enlarged prostate.

Dist. by: Organon LLC, a subsidiary of
ORGANON & Co.,
Jersey City, NJ 07302, USA

For patent information: www.organon.com/our-solutions/patent/

© 2023 Organon group of companies. All rights reserved.

Revised: 11/2023

usppi-og0906-5t-2311r002

PRINCIPAL DISPLAY PANEL - 5 mg Tablet Bottle Label

NDC 78206-153-01

Proscar®
(finasteride) Tablets

5 mg

WARNING: PROSCAR® (finasteride) should
not be used by women or children.
Women who are or may potentially be
pregnant must not use PROSCAR. They
should also not handle crushed or broken
tablets of PROSCAR. (See Package Insert.)

Rx only

30 Tablets